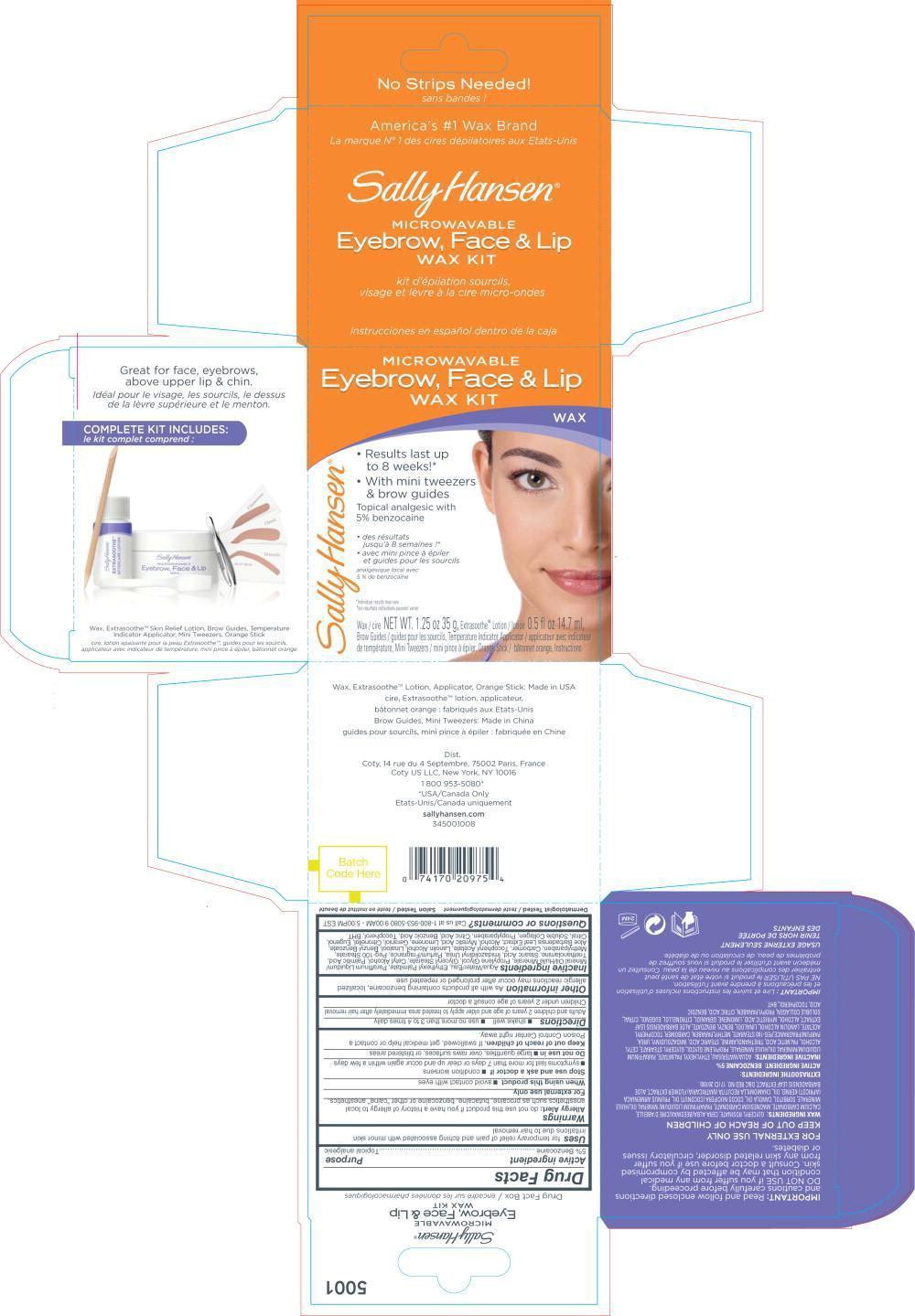 DRUG LABEL: Sally Hansen Microwavable Eybrow, Face and Lip Wax Kit
NDC: 66184-155 | Form: KIT | Route: TOPICAL
Manufacturer: Coty US LLC
Category: otc | Type: HUMAN OTC DRUG LABEL
Date: 20230525

ACTIVE INGREDIENTS: BENZOCAINE 0.05 g/1 g
INACTIVE INGREDIENTS: WATER; ETHYLHEXYL PALMITATE; MINERAL OIL; PROPYLENE GLYCOL; GLYCERYL MONOSTEARATE; CETYL ALCOHOL; PALMITIC ACID; TROLAMINE; STEARIC ACID; IMIDUREA; PEG-100 STEARATE; METHYLPARABEN; .ALPHA.-TOCOPHEROL ACETATE; LANOLIN ALCOHOLS; LINALOOL, (+/-)-; BENZYL BENZOATE; ALOE VERA LEAF; ALCOHOL; MYRISTIC ACID; GERANIOL; .BETA.-CITRONELLOL, (R)-; EUGENOL; CITRAL; PROPYLPARABEN; CITRIC ACID MONOHYDRATE; BENZOIC ACID; TOCOPHEROL; BUTYLATED HYDROXYTOLUENE

Drug Facts

Active ingredient

5% Benzocaine

Purpose

Topical analgesic

Uses

for temporary relief of pain and itching associated with minor skin irritations due to hair removal

Warnings

Allergy Alert: do not use this product if you have a history of allergy to local anesthetics such as procaine, butacaine, benzocaine or other "caine" anesthetics.

For external use only

When using this product

- avoid contact with eyes

Stop use and ask a doctor if

- condition worsens
- symptoms last for more than 7 days or clear up and occur again within a few days

Do not use in

- large quantities, over raws surfaces, or blistered areas

Keep out of reach of children. If swallowed, get medical help or contact a Poison Control Center right away.

Directions

- shake well
- use no more than 3 to 4 times daily

Adults and children 2 years of age and older apply to treated area immediately after hair removal

Children under 2 years of age consult a doctor

Inactive ingredients

Aqua/Water/Eau, Ethylhexyl Palmitate, Paraffinum Liquidum/ Mineral Oil/Huile Minerale, Propylene Glycol, Glyceryl Stearate, Cetyl Alcohol, Palmitic Acid, Triethanolamine, Stearic Acid, Imidazolidinyl Urea, Parfum/Fragrance, Peg-100 Stearate, Methylparaben, Carbomer, Tocopheryl Acetate, Lanolin Alcohol, Linalool, Benzyl Benzoate, Aloe Barbadensis Leaf Extract, Alcohol, Myristic Acid, Limonene, Geraniol, Citronellol, Eugenol, Citral, Soluble Collagen, Propylparaben, Citric Acid, Benzoic Acid, Tocopherol, BHT.

Questions or comments?

Call us at 1-800-953-5080 9:00AM - 5:00PM EST

Principal Display Panel – Kit Label

MICROWABLE
Eyebrow, Face & Lip
WAX KIT

WAX

• Results last up
to 8 weeks!*
• With mini tweezers
& brow guides

Topical analgesic with
5 % benzocaine

• des resultants
jusqu'à 8 semaines !*
• avec mini pince à épiler
et guides pour les sourcils

analgésique local avec
5 % de benzocaïne

*Individual results may vary
*les resultants individuals prevent varier

Wax / cire NET WT. 1.25 oz 35 g, Extrasoothe™ Lotion / lotion 0.5 fl oz 14.7 ml,
Brow Guides / guides pour les sourcils, Temperature Indicator Applicator . applicateur avec indicateur
de temperature, Mini Tweezers / mini pince à épiler, Orange Stick / bâtonnet orange, Instuctions